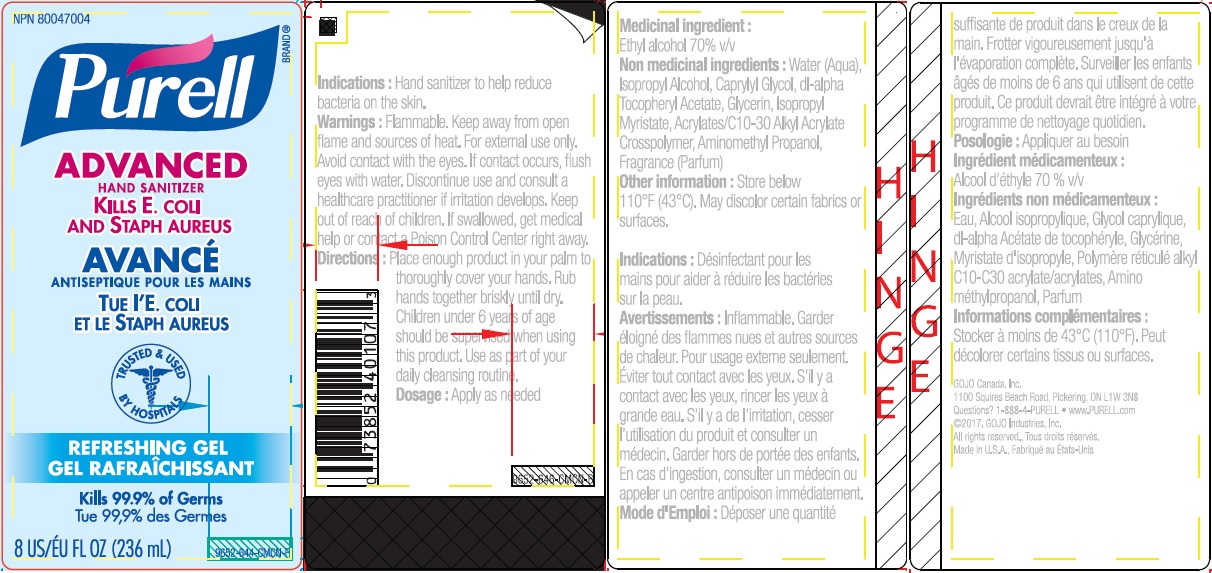 DRUG LABEL: PURELL Advanced Hand Sanitizer Refreshing Gel
NDC: 21749-972 | Form: GEL
Manufacturer: GOJO Industries, Inc.
Category: otc | Type: HUMAN OTC DRUG LABEL
Date: 20250702

ACTIVE INGREDIENTS: ALCOHOL 0.7 mL/1 mL
INACTIVE INGREDIENTS: WATER; ISOPROPYL ALCOHOL; CAPRYLYL GLYCOL; GLYCERIN; ISOPROPYL MYRISTATE; .ALPHA.-TOCOPHEROL ACETATE, D-; AMINOMETHYLPROPANOL

PURELL Advanced Hand Sanitizer Refreshing Gel